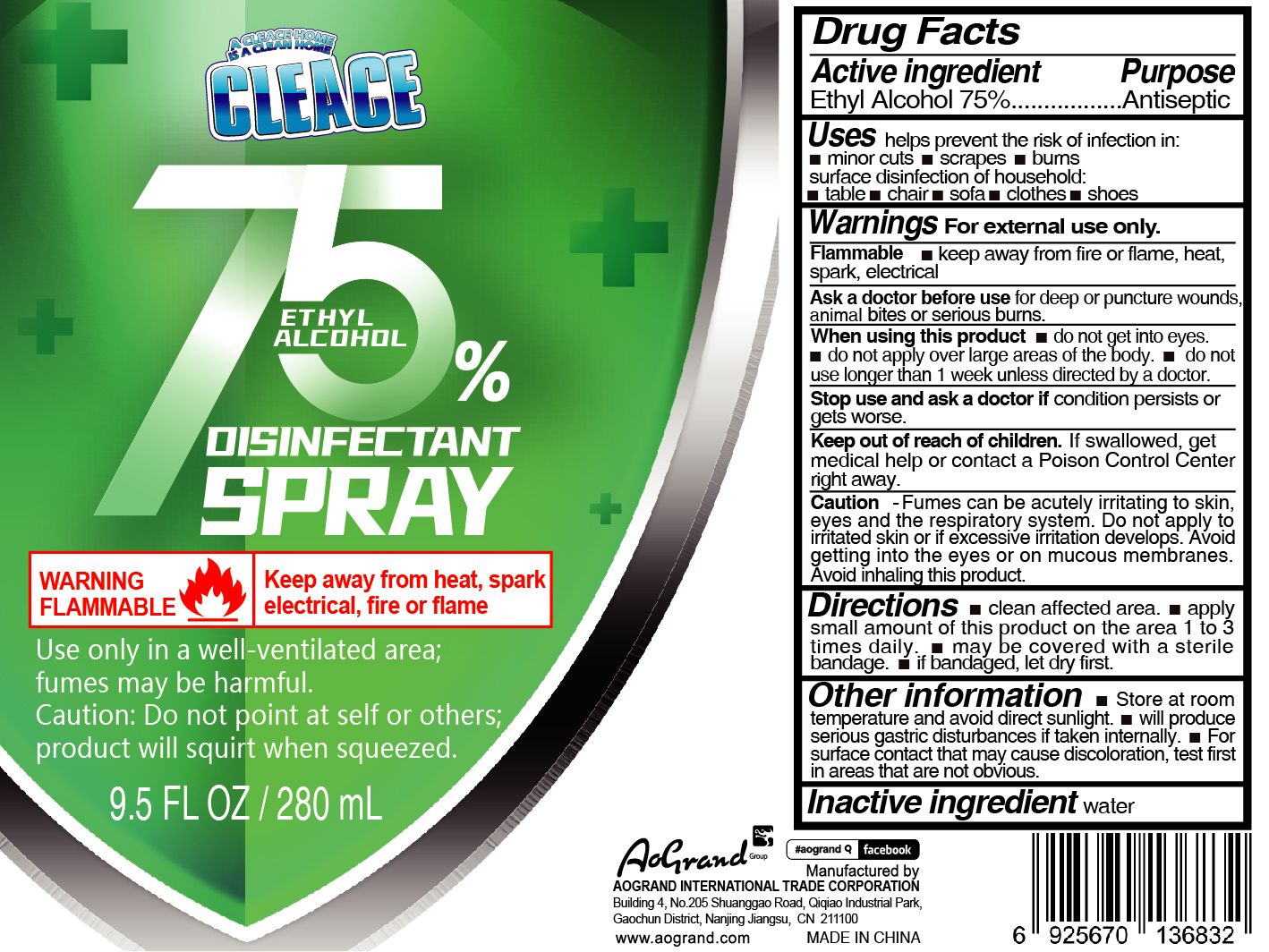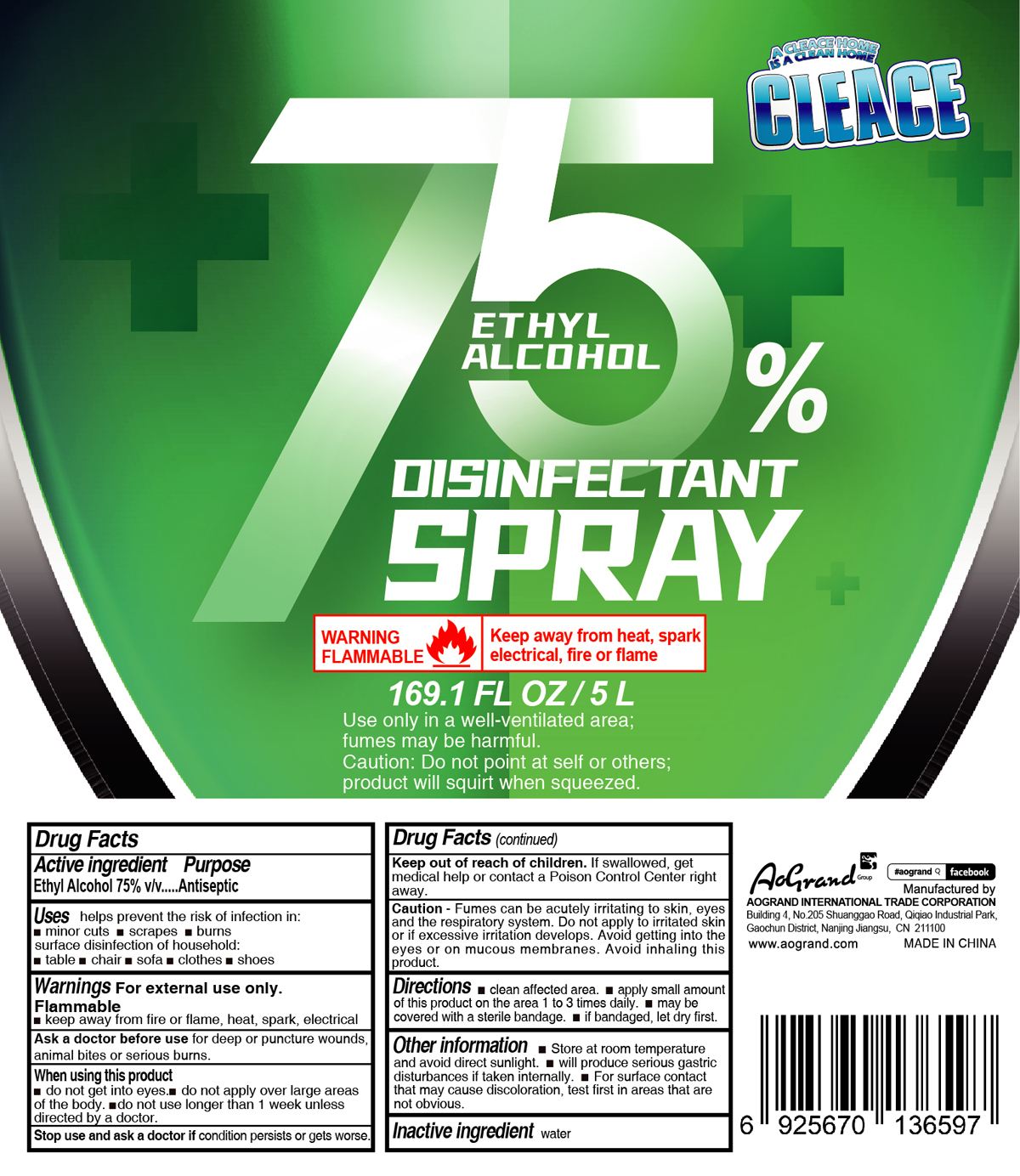 DRUG LABEL: CLEACE Alcohol disinfectant
NDC: 74621-009 | Form: LIQUID
Manufacturer: AOGRAND INTERNATIONAL TRADE CORPORATION
Category: otc | Type: HUMAN OTC DRUG LABEL
Date: 20230211

ACTIVE INGREDIENTS: ALCOHOL 75 mL/100 mL
INACTIVE INGREDIENTS: WATER

CLEACE Alcohol disinfectant

Active Ingredient

Alcohol 75% v/v. Antiseptic

Purpose

Antiseptic

Uses

helps prevent the risk of infection in

- minor cuts
- scrapes
- burns
- surface disinfection of household
- table
- chair
- sofa
- clothes
- shoes

Warnings

For external use only.

Flammable.

Keep away from fire or flame, heat, spark, electrical

Ask a doctor before use

for deep or puncture wounds, animal bites or serious burns

When using this product

- do not get into eyes.
- do not apply over large areas of body
- do not use longer than 1 week unless directed bu a doctor

Stop use and ask a doctor

if condition persists or gets worse.

Keep out of reach of children. Children must be supervised in use of this product.

Caution

Fumes can be acutely irritating to skin, eyes and the respiratory system. Do not apply to irritated skin or if excessive irritation develops. Avoid getting into the eyes or on mucous membranes. Avoid inhaling this product.

Directions

- clean affected area
- apply small amount of this product on the area 1 to 3 times daily
- may be covered with a sterile bandage
- if bandaged, let dry first

Inactive ingredients

water.

Other information

Store at room temperature and avoid direct sunlight

will produce serious gastric disturbances if taken internally

for surface contact that may cause discoloration, test first in areas that are not obvious

Package Label - Principal Display Panel

74621-009-01 280mL

74621-009-02 5000 mL